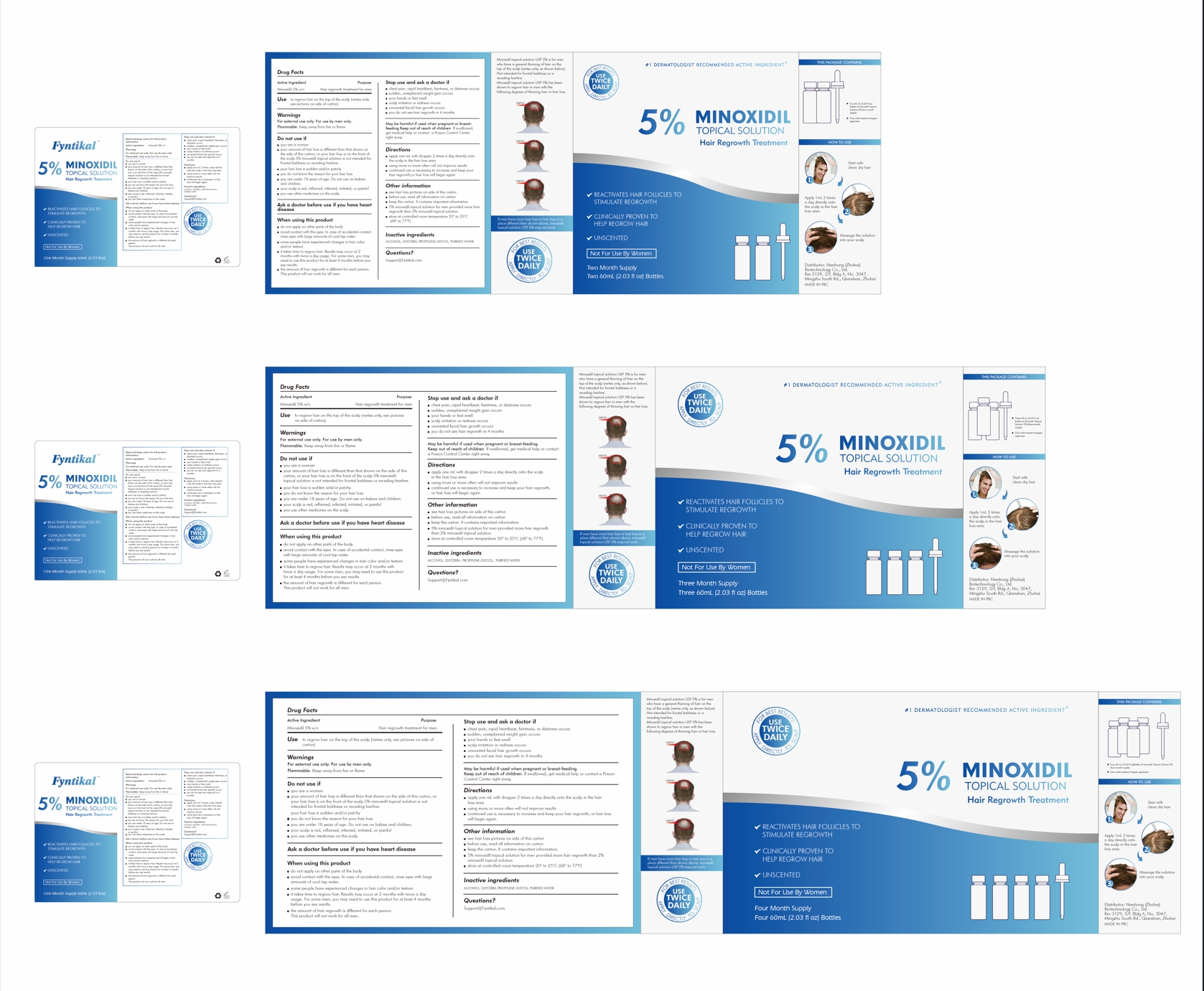 DRUG LABEL: 5% MINOXIDIL TOPICAL Solution
NDC: 85174-001 | Form: SOLUTION
Manufacturer: Nanhong (Zhuhai) Biotechnology Co., Ltd.
Category: otc | Type: HUMAN OTC DRUG LABEL
Date: 20250115

ACTIVE INGREDIENTS: MINOXIDIL 5 g/100 mL
INACTIVE INGREDIENTS: GLYCERIN; ALCOHOL; WATER; PROPYLENE GLYCOL

5% MINOXIDIL TOPICAL SOLUTION

5% MINOXIDIL TOPICAL SOLUTION

ACTIVE INGREDIENT

MINOXIDIL 5%

PURPOSE

Hair regrowth treatment for men

INDICATIONS AND USAGE

to regrow hair on the top of the scalp (vertex onlysee pictures on side of carton)

WARNINGS

For external use only. For use by men only.

Flammable: Keep away from fire or flame

DO NOT USE

you are a woman
your amount of hair loss is different than that shown onthe side of this carton, or your hair loss is on the front ofthe scalp.5% minoxidil topical solution is not intended forfrontal baldness or receding hairline.

your hair loss is sudden and/or patchy

you do not know the reason for your hair loss

you are under 18 years of age. Do not use on babiesand children.

your scalp is red, inflamed, infected, irritated, or painful

you use other medicines on the scalp

WHEN USING

do not apply on other parts of the body

avoid contact with the eyes. In case of accidental contactrinse eyes with large amounts of cool tap water.

some people have experienced changes in hair color and/or texture

it takes time to regrow hair. Results may occur at 2months with twice a day usage. For some men, you mayneed to use this product for at least 4 months before yousee results.

the amount of hair regrowth is different for each person.This product will not work for all men.

STOP USE

chest pain, rapid hearbeat, faintness, or dizziness occurs

sudden, unexplained weight gain occurs

your hands or feet swell

scalp irritation or redness occurs

unwanted facial hair growth occursyou do not see hair regrowth in 4 months

KEEP OUT OF REACH OF CHILDREN

May be harmful if used when pregnant or breast-feeding.Keep out of reach of children. lf swallowedget medical help or contact a Poison Control Centerright away.

DOSAGE AND ADMINISTRATION

apply one mL with dropper 2 times a day directly ontothe scalp in the hair loss area

using more or more often will not improve results

continued use is necessary to increase and keep yourhair regrowth,or hair loss will begin again

STORAGE AND HANDLING

see hair loss pictures on side of this carton

before use, read all information on carton

keep the carton. lt contains important information.

5% minoxidil topical solution for men provided more hairregrowth than 2% minoxidil topical solution

store at controlled room temperature 20° to 25°C(68° to 77°F)

INACTIVE INGREDIENT

ALCOHOL
GLYCERIN
PROPYLENE GLYCOL
PURIFIED WATER